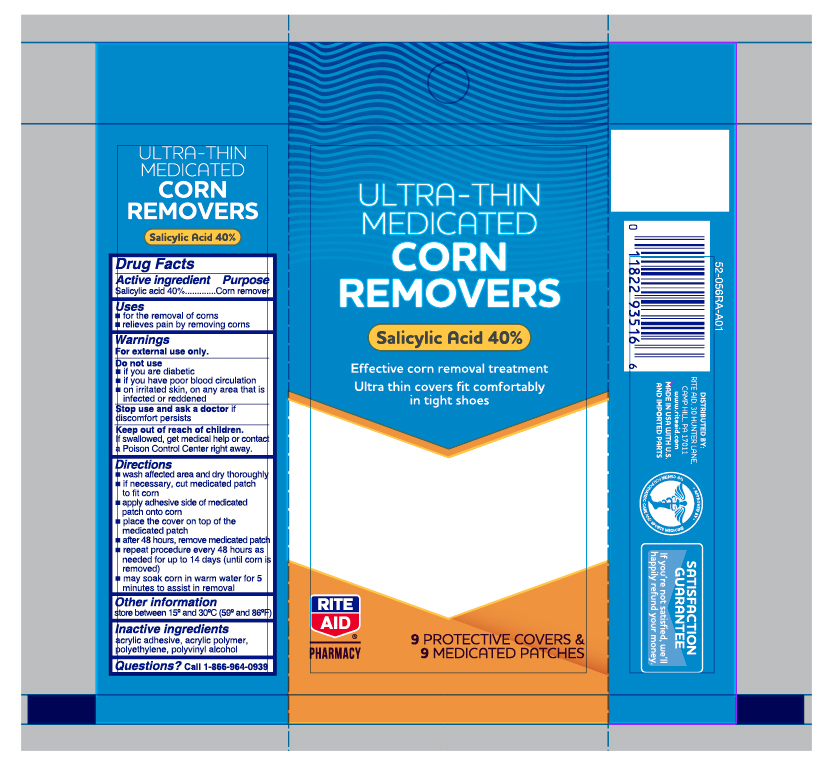 DRUG LABEL: Salicylic Acid
NDC: 11822-0132 | Form: PATCH
Manufacturer: Rite Aid Corporation
Category: otc | Type: HUMAN OTC DRUG LABEL
Date: 20250621

ACTIVE INGREDIENTS: SALICYLIC ACID 40 mg/9 1
INACTIVE INGREDIENTS: POLYVINYL ALCOHOL; VINYL ACETATE; HIGH DENSITY POLYETHYLENE

Rite Aid Ultra Thin Corn Removers

Active ingredient

Salicylic acid 40%

Purpose

Corn remover

Use

- for the removal of corns
- relieves pain by removing corns

Warnings

For external use only.

Do not use

- if you are a diabetic
- if you have poor blood circulation
- on irritated skin, on any area that is infected or reddened

Stop use and ask a doctor

if discomfort persists

Keep out of the reach of children

If swallowed, get medical help or contact a Poison Control Center right away.

Directions

- wash affected area and dry area thoroughly
- if necessary, cut medicated patch to fit corn
- apply adhesive side of medicated patch onto corn
- place the cover on top of the medicated patch
- after 48 hours, remove medicated patch
- repeat procedure every 48 hours as needed for up to 14 days (until corn is removed)
- may soak corn in warm water for 5 minutes to assist in removal

Other information

store between 15° to 30°C (59° to 86°F)

Inactive ingredients

acrylic adhesive, acrylic polymer, polyethylene, polyvinyl alcohol

Questions?

1-866-964-0939

Principal Display Panel

Rite Aid Pharmacy

MAXIMUM STRENGTH

Corn Removers
Ultra Thin
Salicylic acid

- Therapeutic corn removal
- Specifically designed for tight shoes
- Helps relieve painful shoe pressure and friction

9 Medicated Patches/ 9 Pads